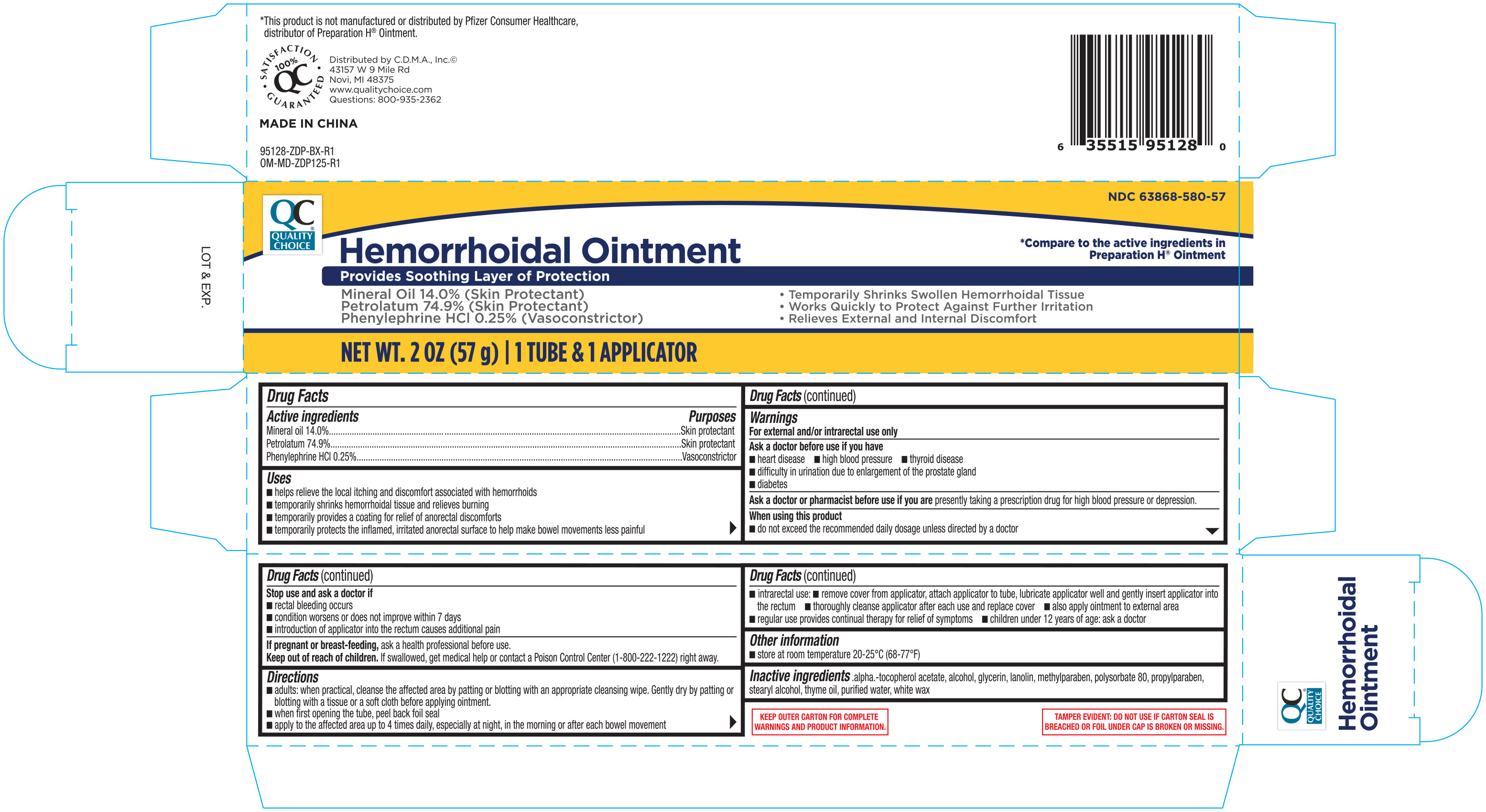 DRUG LABEL: Quality Choice Hemorrhoidal
NDC: 63868-580 | Form: OINTMENT
Manufacturer: Chain Drug Marketing Association
Category: otc | Type: HUMAN OTC DRUG LABEL
Date: 20200218

ACTIVE INGREDIENTS: MINERAL OIL 140 mg/100 g; PETROLATUM 749 mg/100 g; PHENYLEPHRINE HYDROCHLORIDE 2.5 mg/100 g
INACTIVE INGREDIENTS: GLYCERIN; LANOLIN; METHYLPARABEN; ALCOHOL; STEARYL ALCOHOL; THYME OIL; ALPHA-TOCOPHEROL ACETATE; WATER; WHITE WAX; PROPYLPARABEN; POLYSORBATE 80

QC Hemorrhoidal Ointment 2oz (with applicator) NBE Preparation H 95128 ZDP

Active ingredients Purpose

Mineral oil 14%................................................................Protectant

Petrolatum 74.9%............................................................Protectant

Phenylephrine HCl 0.25%..........................................Vasoconstrictor

Uses

- helps relieve the local itching and discomfort associated with hemorrhoids
- temporarily shrinks hemorrhoidal tissue and relieves burning
- temporarily provides a coating for relief of anorectal discomforts
- temporarily protects the inflamed, irritated anorectal surface to help make bowel movements less painful

Warnings For external and/or intrarectal use only

Ask a doctor before use if you have

- heart disease
- high blood pressure
- thyroid disease
- diabetes
- trouble urinating due to an enlarged prostate gland

Ask a doctor or a pharmacist before use if you are now taking a prescription drug for high blood pressure or depression

When using this product do not use more than the recommended daily dosage unless directed by a doctor

Stop use and ask a doctor if

- bleeding occurs
- condition gets worse or does not get better within 7 days
- introduction of the applicator into the rectum causes additional pain

PREGNANCY OR BREAST FEEDING

If pregnant or breast-feeding, ask a physician before use.

Keep out of reach of children. If swallowed, get medical help or contact a Poison Control Center right away.

Directions

- adults: when practical, cleanse the affected area by patting or blotting with an appropriate cleansing wipe. Gently dry by patting or blotting with a tissue or a soft cloth before applying ointment.
- when first opening the tube, peel back foil seal
- apply to the affected area up to 4 times daily, especially at night, in the morning or after each bowel movement
- intrarectal use:
- remove cover from applicator, attach applicator to tube, lubricate applicator well and gently insert applicator into the rectum
- thoroughly cleanse applicator after each use and replace cover
- also apply ointment to external area
- regular use provides continual therapy for relief of symptoms
- children under 12 years of age: ask a doctor

Other information store at 20° to 25°C (68° to 77°F)

INACTIVE INGREDIENT

Inactive ingredients .alpha.-tocopherol acetate, alcohol, glycerin, lanolin, methylparaben, polysorbate 80, propylparaben, alcohol, thyme oil, purified water, white wax

DOSAGE AND ADMINISTRATION

Distributed by:

C.D.M.A., Inc.

43157 W. Nine Mile

Novi, MI 48376-0995

www.qualitychoice.com

Made in China